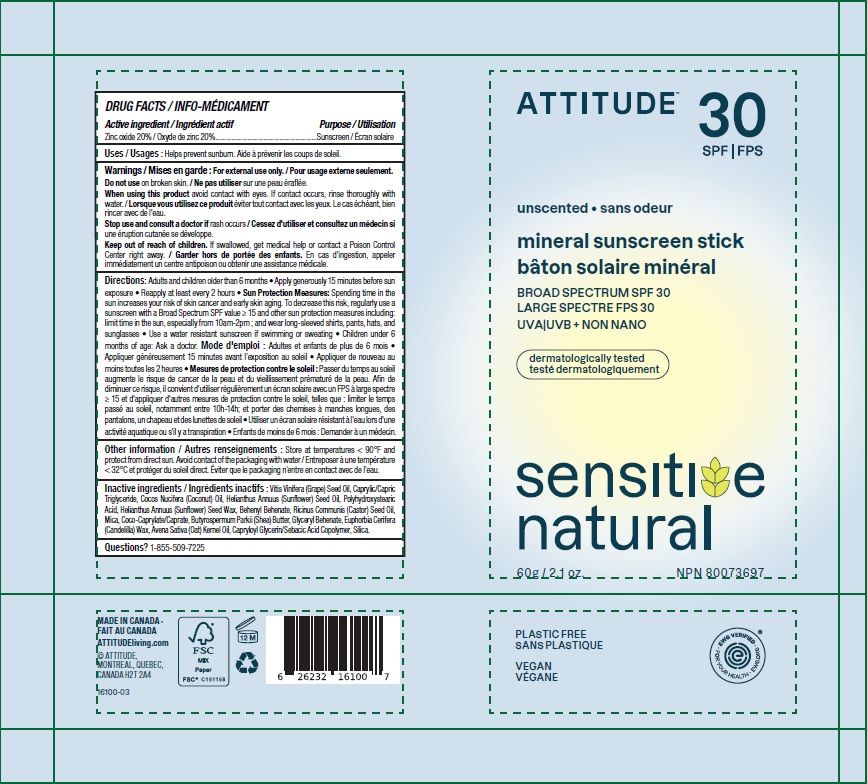 DRUG LABEL: ATTITUDE Oatmeal Sensitive Natural Mineral Sunscreen Stick Unscented SPF 30
NDC: 61649-100 | Form: STICK
Manufacturer: 9055-7588 Quebec Inc. DBA Attitude
Category: otc | Type: HUMAN OTC DRUG LABEL
Date: 20241209

ACTIVE INGREDIENTS: ZINC OXIDE 20 g/100 g
INACTIVE INGREDIENTS: GRAPE SEED OIL; SUNFLOWER OIL; CANDELILLA WAX; COCONUT OIL; CASTOR OIL; MICA; HELIANTHUS ANNUUS SEED WAX; CAPRYLOYL GLYCERIN/SEBACIC ACID COPOLYMER (2000 MPA.S); POLYHYDROXYSTEARIC ACID (2300 MW); SILICON DIOXIDE; GLYCERYL MONOBEHENATE; BEHENYL BEHENATE; MEDIUM-CHAIN TRIGLYCERIDES; OAT KERNEL OIL; SHEA BUTTER; COCO-CAPRYLATE/CAPRATE

ATTITUDE Oatmeal Sensitive Natural Mineral Sunscreen Stick - Unscented - SPF 30

DRUG FACTS

ACTIVE INGREDIENT

Zinc oxide (20 %)

PURPOSE

Sunscreen

INDICATIONS AND USAGE

Helps prevent sunburn.

WARNINGS

For external use only.

Do not use on broken skin.

When using this product avoid contact with eyes. If contact occurs, rinse thoroughly with water.

Keep out of reach of children. If swallowed, get medical help or contact a Poison Control Center right away.

Stop use and consult a doctor if rash occurs.

DOSAGE AND ADMINISTRATION

Adults and children older than 6 months.

- Apply generously 15 minutes before sun exposure.
- Reapply at least every 2 hours.
- Sun Protection Measures: Spending time in the sun increases your risk of skin cancer and early aging. To decrease this risk, regularly use a sunscreen with a Broad Spectrum SPFvalue of 15 or higher and other sun protection measures including: limit time in the sun, especially from 10am-2pm; and wear long-sleeved shirts, pants, hats and sunglasses.
- Use a water resistant sunscreen if swimming or sweating.
- Children under 6 months of age: Ask a doctor.

STORAGE AND HANDLING

Store at temperatures < 90F and protect from direct sun. Avoid contact of packaging with water.

INACTIVE INGREDIENT

Vitis Vinifera (Grape) Seed Oil, Caprylic/Capric Triglyceride, Cocos Nucifera (Coconut) Oil, Helianthus Annuus (Sunflower) Seed Oil, Polyhydroxystearic Acid, Helianthus Annuus (Sunflower) Seed Wax, Behenyl Behenate, Ricinus Communis (Castor) Seed Oil, Mica, Coco-Caprylate/Caprate, Butyrospermum Parkii (Shea) Butter, Glyceryl Behenate, Euphorbia Cerifera (Candelilla) Wax, Avena Sativa (Oat) Kernel Oil, Capryloyl Glycerin/Sebacic Acid Copolymer, Silica.

Questions ? 1-855-509-7225

PACKAGE LABEL

ATTITUDE

natural care

SPF 30

unscented

mineral sunscreen stick

BROAD SPECTRUM SPF 30

UVA UVB + NON NANO

Oatmeal Sensitive Natural

Plastic free suncare

60 g / 2.1 oz.

NPN 80073697

Vegan

EWG Verified

Ocean Lovers

Plastic Free

Dermatologically tested